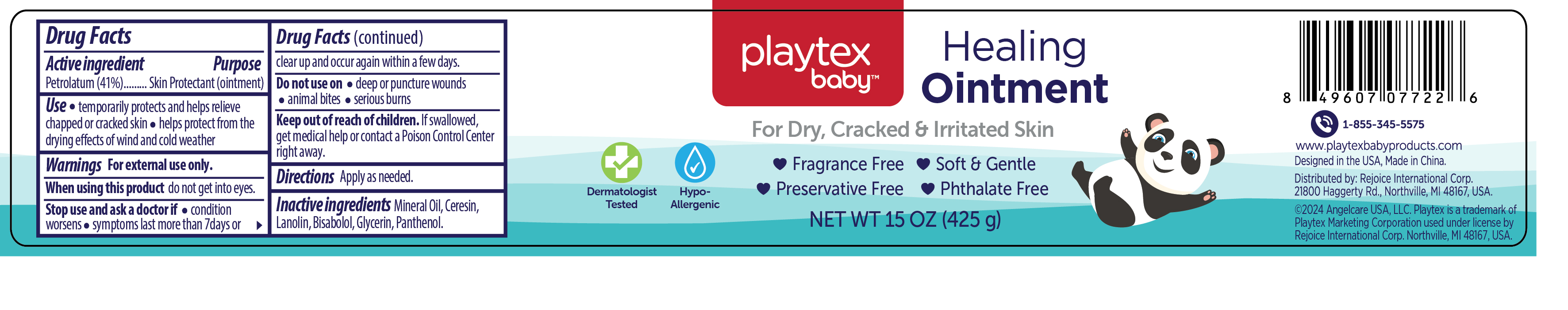 DRUG LABEL: Healing Cream15oz
NDC: 57337-171 | Form: OINTMENT
Manufacturer: Rejoice International Corp.
Category: otc | Type: HUMAN OTC DRUG LABEL
Date: 20240911

ACTIVE INGREDIENTS: PETROLATUM 41 g/100 g
INACTIVE INGREDIENTS: GLYCERIN; CERESIN; LEVOMENOL; PANTHENOL; MINERAL OIL; LANOLIN

Healing Cream15oz

Active ingredient

Petrolatun 41%

Purpose

Skin Protectant (Ointment)

Use

- temporarily protects and helps relieve chapped or cracked skin
- helps protect from the drying effects of wind and cold weather

Warnings

For external use only

When using this product do not get into eyes.

Stop use and ask a doctor if

- condition worsens
- symptoms last more than 7days or clear up and occur again within a few days.

Do not use on

- deep or puncture wounds
- animal bites
- serious burns

Keep out of reach of children

If swallowed, get medical help or contact a Poison Control Center right away.

Directions

Apply as needed.

Inactive ingredients

Mineral Oil

Ceresin

Lanolin

Bisabolol

Glycerin

Panthenol